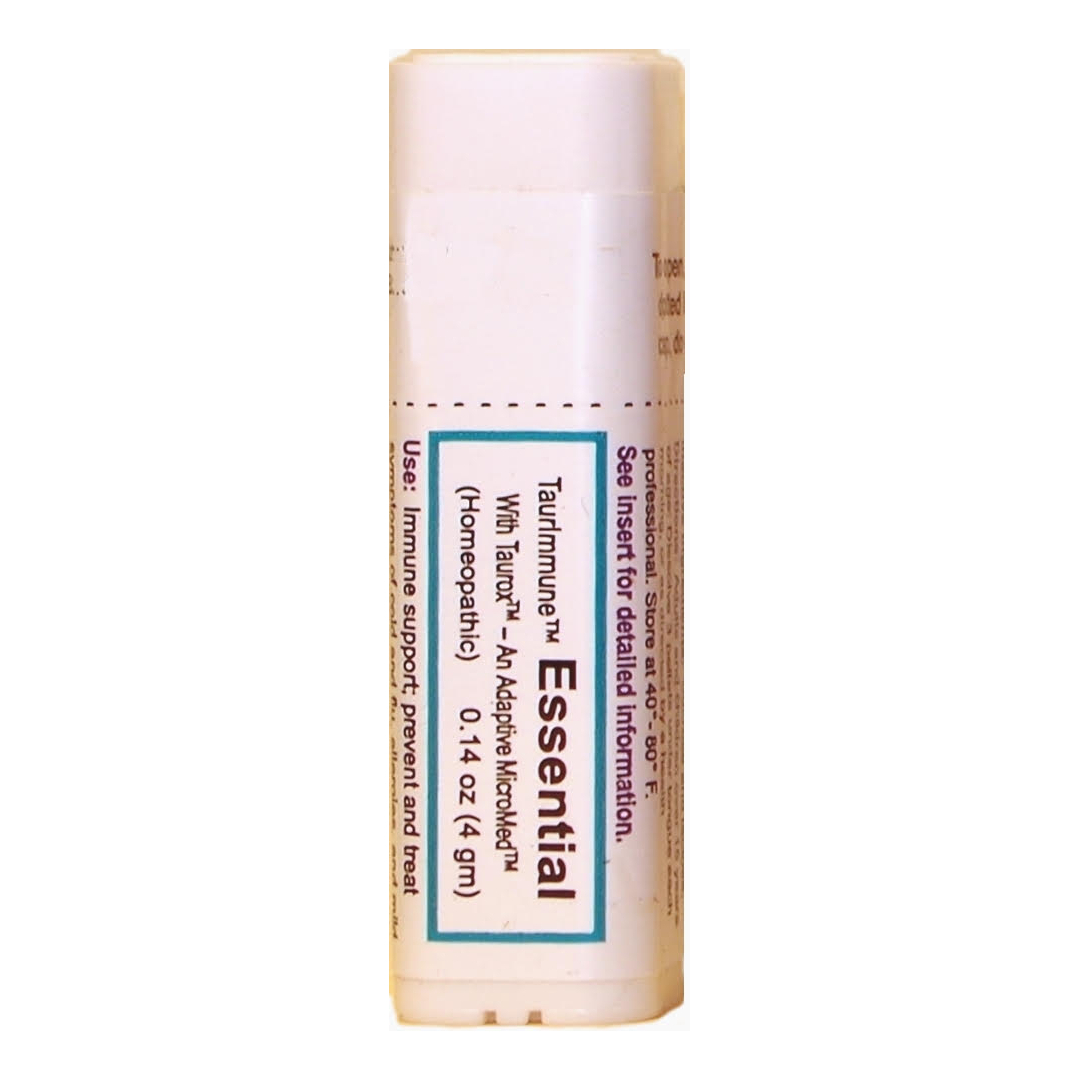 DRUG LABEL: TaurImmune Essential
NDC: 73311-109 | Form: PELLET
Manufacturer: CureImmune Corp.
Category: homeopathic | Type: HUMAN OTC DRUG LABEL
Date: 20190826

ACTIVE INGREDIENTS: ZINC 8 [hp_X]/1 1; POTASSIUM CARBONATE 8 [hp_X]/1 1; SELENIUM 8 [hp_X]/1 1; ZINC CARBOBENZOXY-.BETA.-ALANYLTAURINATE 4 [hp_X]/1 1; SILICON DIOXIDE 8 [hp_X]/1 1; PHOSPHORIC ACID 8 [hp_X]/1 1
INACTIVE INGREDIENTS: SUCROSE; LACTOSE, UNSPECIFIED FORM

Taurimmune Essential

Active Ingredients

Tauroxicum (COBAT) 4X (13.6%), 12X (1.5%), 30X (1.5%).

Kali carbonicum 8X (13.6%), 12X (1.5%), 30X (1.5%)

Phosphoricum acidum 8X (13.6%), 12X (1.5%), 30X (1.5%)

Selenium metallicum 8X (13.6%), 12X (1.5%), 30X (1.5%)

Silicea 8X (13.6%), 12X (1.5%), 30X (1.5%)

Zincum metallicum 8X (13.6%), 12X (1.5%), 30X (1.5%)

Use

For Immune support, and treatment of mild fatigue, allergies, colds, and flu.

PURPOSE

For Immune support, and treatment of mild fatigue, allergies, colds, and flu.

Directions

Directions for adults and children 15 years of age and older: Dissolve three pellets under tongue each morning, or as directed by a health professional. Best if taken early in the day, at least 5 minutes before or after eating. See package insert for details.

Warnings

Keep out of reach of children. Do not use if you are pregnant or breast feeding, an organ recipient, using immunosuppressive drugs, or if the tamper-evident seal is broken or missing. See package insert for details.

Keep out of reach of children.

Inactive Ingredients

Sucrose (80%), Lactose (20%).

Disclaimer

Claims based on traditional
homeopathic practice, not accepted
medical evidence. Not FDA evaluated.

PACKAGE LABEL

TaurImmune Essential

With Taurox, An Adaptive MicroMed

Homeopathic

0.14 oz (4 gm)